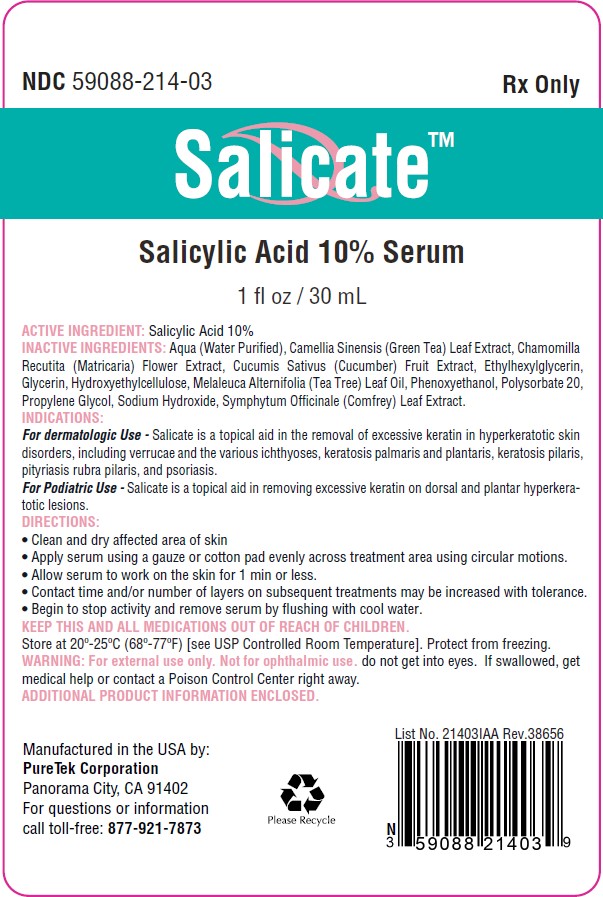 DRUG LABEL: Salicate
NDC: 59088-214 | Form: GEL
Manufacturer: PureTek Coproration
Category: prescription | Type: HUMAN PRESCRIPTION DRUG LABEL
Date: 20231013

ACTIVE INGREDIENTS: SALICYLIC ACID 10 mg/100 mL
INACTIVE INGREDIENTS: GREEN TEA LEAF; CUCUMBER; GLYCERIN; HYDROXYETHYL CELLULOSE, UNSPECIFIED; PHENOXYETHANOL; POLYSORBATE 20; PROPYLENE GLYCOL; SODIUM HYDROXIDE; CHAMOMILE; ETHYLHEXYLGLYCERIN; MELALEUCA ALTERNIFOLIA (TEA TREE) LEAF OIL; WATER; COMFREY LEAF

Salicate
Salicylic Acid 10% Serum

Salicate™

Salicylic Acid, 10%

Rx Only

For Topical Dermatological Use Only, not for ophthalmic, oral, or intravaginal use.

Description:

Salicate™ is applied topically and used to remove excessive keratin in hyperkeratotic skin disorders. Each gram of Salicate™ contains salicylic acid 10% as the active ingredient and the following inactive ingredients: Aqua (Water Purified), Camellia Sinensis (Green Tea) Leaf Extract, Chamomilla Recutita (Matricaria) Flower Extract, Cucumis Sativus (Cucumber) Fruit Extract, Ethylhexylglycerin, Glycerin, Hydroxyethylcellulose, Melaleuca Alternifolia (Tea Tree) Leaf Oil, Phenoxyethanol, Polysorbate 20, Propylene Glycol, Sodium Hydroxide, Symphytum Officinale (Comfrey) Leaf Extract.

Clinical Pharmacology:

Salicylic acid has been shown to produce desquamation of the horny layer of skin while not affecting qualitative or quantitative changes in the structure of the viable epidermis^1,2. The mechanism of action has been attributed to the dissolution of intercellular cement substances^3. In a study of the percutaneous absorption of salicylic acid 6% in four patients with extensive active psoriasis, Taylor and Halprin^4 showed that peak serum salicylate levels never exceeded 5 mg/100 ml even though more than 60% of the applied salicylic acid was absorbed. Systemic toxic reactions are usually associated with higher serum levels (30 to 40 mg/100 ml). Peak serum levels occurred within 5 hours of the topical application under occlusion. The sites were occluded for 10 hours over the entire body surface below the neck. Since salicylates are distributed in the extracellular space, patients with a contracted extracellular space due to dehydration or diuretics have higher salicylate levels than those with common extracellular space. (See PRECAUTIONS).

The primary metabolites identified in the urine after topical administration are salicyluric acid (52%), salicylate glucuronides (42%), and free salicylic acid (6%). The urinary metabolites after percutaneous absorption differ from those after oral salicylate administration; those derived from percutaneous absorption contain more glucuronides and less salicyluric and salicylic acid. Almost 95% of a single dose of salicylate is excreted within 24 hours of its entrance into the extracellular space. Fifty to eighty percent of salicylate is protein bound to albumin. Salicylates compete with the binding of several drugs and can modify the action of these drugs. By similar competitive mechanisms, other drugs can influence salicylate serum levels. (See PRECAUTIONS).

Contraindications Section:

Salicate™ should not be used in any patient known to be sensitive to salicylic acid or any other listed ingredients.

Indications & Usage:

For dermatologic Use

Salicate™ is a topical aid in the removal of excessive keratin in hyperkeratotic skin disorders, including verrucae and the various ichthyoses, keratosis palmaris and plantaris, keratosis pilaris, pityriasis rubra pilaris, and psoriasis.

For Podiatric Use

Salicate™ is a topical aid in removing excessive keratin on dorsal and plantar hyperkeratotic lesions.

Warnings:

Salicate™ is for external use only. It is not for ophthalmic, oral, anal, or intravaginal use. Contact with eyes, lips, broken or inflamed skin, and mucous membranes should be avoided. Salicate™ should not be used by persons who have a known hypersensitivity to salicylic acid or other listed ingredients. Prolonged use over large areas, especially in children and those patients with significant renal or hepatic impairment, could result in salicylism. Concomitant use of other drugs which may contribute to elevated serum salicylate levels should be avoided where the potential for toxicity is present. In children under 12 years of age and those patients with renal or hepatic impairment, the area to be treated should be limited, and the patient should be monitored closely for signs of salicylate toxicity: nausea, vomiting, dizziness, loss of hearing, tinnitus, lethargy, hyperpnoea, diarrhea, psychic disturbances.

In the event of salicylic acid toxicity, Salicate™ should be discontinued. Fluids should be administered to promote urinary excretion. Treatment with sodium bicarbonate (oral or intravenous) should be instituted as appropriate. Considering the potential risk of developing Reye's syndrome, salicylate products should not be administered to children or teenagers with varicella or influenza, unless directed by a physician. When using this product, skin irritation and dryness is more likely to occur if you use another topical acne medication at the same time. If irritation occurs, only use one topical acne medication at a time. Applying the serum more than once per week will increase the risk of skin sensitivity.

Precautions:

Salicate™ should be used only as directed by a physician and should not be used to treat any condition other than that for which it is prescribed. Salicate™ should not be used on any skin area where inflammation or exudation is present as increased absorption may occur. If redness or irritation occurs, discontinue use and consult with prescribing physician.

Drug Interactions:

The following interactions are from a published review^5 and include reports concerning oral and topical salicylate administration. The relationship of these interactions to the use of SALICYLIC ACID is not known.

A. Due to the competition of salicylate with other drugs for binding to serum albumin the following drug interactions may occur:
Drug | Description of Interaction
Tolbutamide; Sulfonylureas | Hypoglycemia potentiated
Methotrexate | Decreases tubular reabsorption; clinical toxicity from methotrexate can result
Oral Anticoagulants | Increased bleeding
B. Drugs changing salicylate levels by altering renal tubular reabsorption:
Drug | Description of Interaction
Corticosteroids | Decreases plasma salicylate level; tapering doses of steroids may promote salicylism
Ammonium Sulfate | Increases plasma salicylate level
C. Drugs with complicated interactions with salicylates:
Drug | Description of Interaction
Heparin | Salicylate decreases platelet adhesiveness and interferes with hemostasis in heparin-treated patients
Pyrazinamide | Inhibits pyrazinamide-induced hyperuricemia
Uricosuric Agents | Effect of probenecid, sulfinpyrazone, and phenylbutazone inhibited
D. The following alterations of laboratory tests have been reported during salicylate therapy:^6
Laboratory Tests | Effect of Salicylates
Thyroid Function | Decreased PBI; increased T uptake
Urinary Sugar | False negative with glucose oxidase; false positive with Clinitest with high-dose salicylate therapy (2-5g qd)
5 Hydroxyindole Acetic Acid | False negative with fluorometric test
Acetone, Ketone Bodies | False positive FeCl in Gerhardt reaction; red color persists with boiling
17-OH corticosteroids | False reduced values with >4.8 g qd salicylate
Vanilmandelic Acid | False reduced values
Uric Acid | May increase or decrease depending on the dose
Prothrombin | Decreased levels; slightly increased prothrombin time

Pregnancy:

Pregnancy (Category C)

Salicylic acid is teratogenic in rats and monkeys. It is difficult to extrapolate from oral doses of acetylsalicylic acid used in these studies to topical administration as the oral dose to monkeys may represent four times the Maximum daily human dose of salicylic acid when applied topically over a large body surface. There are no adequate and well-controlled studies in pregnant women. Salicate™ should be used during pregnancy only if the potential benefit justifies the risk to the fetus.

Nursing Mothers

It is unknown whether topically applied salicylic acid is excreted in human milk. Since many drugs are excreted in human milk, caution should be exercised by physicians when administering Salicate™ to nursing mothers and nursing mothers should certainly not apply Salicate™ to the chest area or any other part of the body with which the nursing child's mouth is likely to come in contact. Because of the potential for serious adverse reactions in nursing infants from the mother's use of Salicate™, a decision should be made whether to discontinue nursing or to discontinue the drug, taking into account the importance of the drug to the mother.

Carcinogenesis, Mutagenesis, Impairment of Fertility

No data are available concerning the potential carcinogenic or reproductive effects of Salicate™. It has been shown to lack mutagenic potential in the Ames Salmonella test.

Adverse Reactions:

Transient stinging, burning, itching or irritation is possible. Peeling of the skin may increase as the salicylic acid works to loosen excess keratin. If excessive burning, stinging or peeling occurs, discontinue use and consult your physician.

Dosage & Administration:

Clean and dry affected area of skin, then apply Salicate™ ™ serum over the affected skin once daily, or as directed by healthcare provider. Apply serum using a gauze or cotton pad evenly across treatment area using circular motions. Allow serum to work on the skin for 1 min or less. Use a sunscreen, wear protective clothing, and limit sun exposure while using this product and for a week afterwards. You will experience a stinging or tingling sensation. If excessive stinging or discomfort occurs, neutralize the serum by flushing the skin with cool water. Redness may occur for a short period of time, especially for those with sensitive skin types. If redness persists longer than 20-30 minutes, decrease the contact time of the serum or discontinue use.

Stop Use and Ask a Doctor If
• Excessive facial irritation or redness occurs 48-72 hours after application
• Chest pain, faintness, or dizziness occurs
• You experience pain, swelling, or severe burns
• You experience an allergic reaction
• Your skin becomes infected
• If swallowed, seek medical help or contact a Poison Control Center Immediately
*These statements have not been evaluated by the Food and Drug Administration. This product is not intended to treat, cure, prevent, mitigate or diagnose any disease or effect the structure or function of the human body.

How Supplied:

Salicate™ is a serum supplied in a 1 fl oz Bottle. NDC 59088-214-03

REFERENCES:

1. Davies M, Marks R: Br J Dermatol 95: 187-192, 1976. 2. Mars R, Davies M, Cattel A: J Invest Dermatol 64: 283, 1975. 3. Huber C, Christophers E: Arch Derm Res 257: 293-297, 1977. 4. Taylor JR, Halprin KM: Arch Dermatol 111: 740-743, 1975. 5. Goldsmith
LA: Int J Dermatol 18: 32-36. 6. Wilson JG, Ritter EJ, Scott WJ, Fradlein R: Tox Appl Pharmacol 41: 67-78, 1977.

Storage And Handling:

KEEP THIS AND ALL MEDICATIONS OUT OF REACH OF CHILDREN.
Store at 20°-25°C (68°-77°F) [see USP Controlled Room Temperature]. Protect from freezing.

Manufactured in the USA by:
PureTek Corporation
Panorama City, CA 91402
For questions or information
call toll-free: 877-921-787